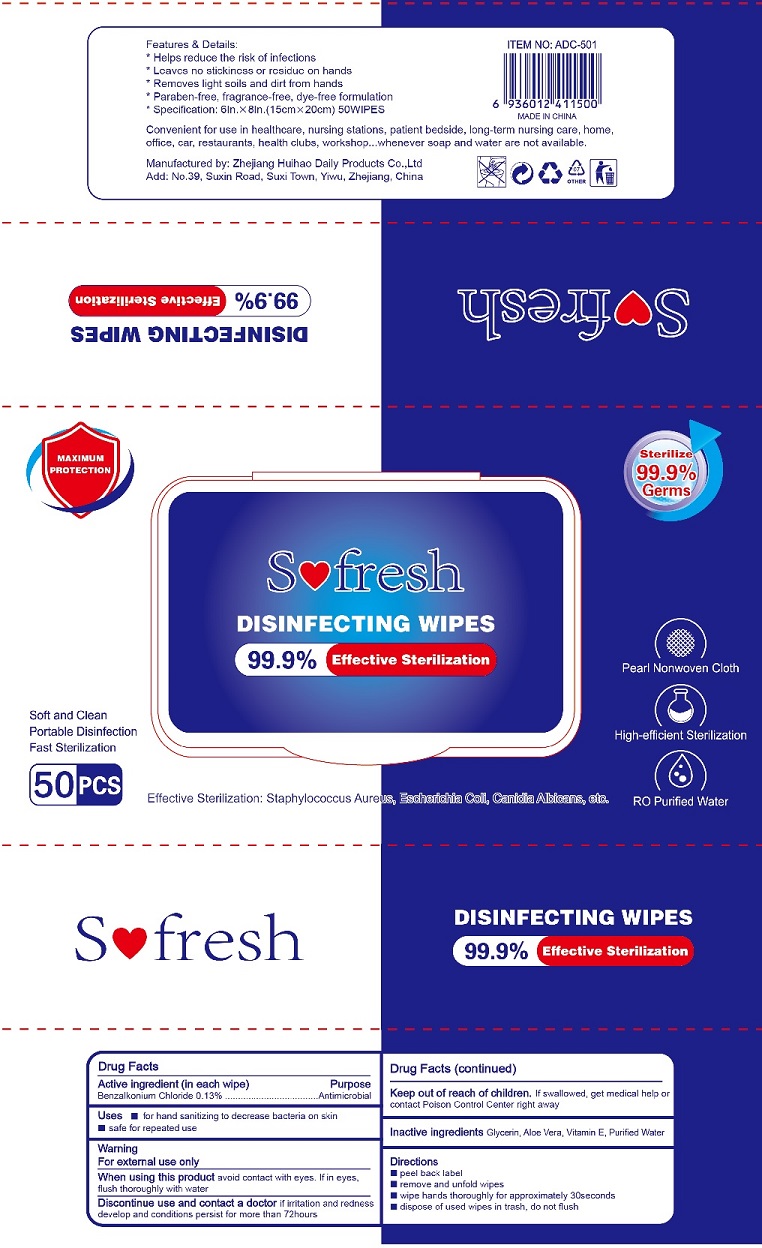 DRUG LABEL: Sofresh Disinfecting Wipes
NDC: 77909-002 | Form: SWAB
Manufacturer: Zhejiang Huihao Daily Products Co.,Ltd
Category: otc | Type: HUMAN OTC DRUG LABEL
Date: 20200518

ACTIVE INGREDIENTS: BENZALKONIUM CHLORIDE 0.13 g/100 g
INACTIVE INGREDIENTS: water; GLYCERIN; ALOE VERA LEAF; ALPHA-TOCOPHEROL

Antibacterial Wipes

Active Ingredient

BENZALKONIUM CHLORIDE 0.13%

Purpose

Antimicrobial

USES

- for hand sanitizing to decrease bacteria on skin
- safe for repeated use

Warning

- For external use only.
- When using this product, avoid contact with eyes. If in eyes, flush thoroughly with water

- Discontinue use and contact a doctor If irritation and redness develop and conditions persist for more than 72 hours

Other Information：

Store below 110℉ (43 ℃); May discolor certain fabrics or surface

KEEP OUT OF REACH OF CHILDREN

●If swallowed, get medical help or contact a Poison Contrl Center right away.

Directions

- peel back label
- remove and unfold wipes
- wipe hards thoroughly for approximately 30 seconds
- dispose of used wipes in trash, do not flush

Inactive ingredients

Glycerin, Aloe vera, Vitamin E, Purified Water